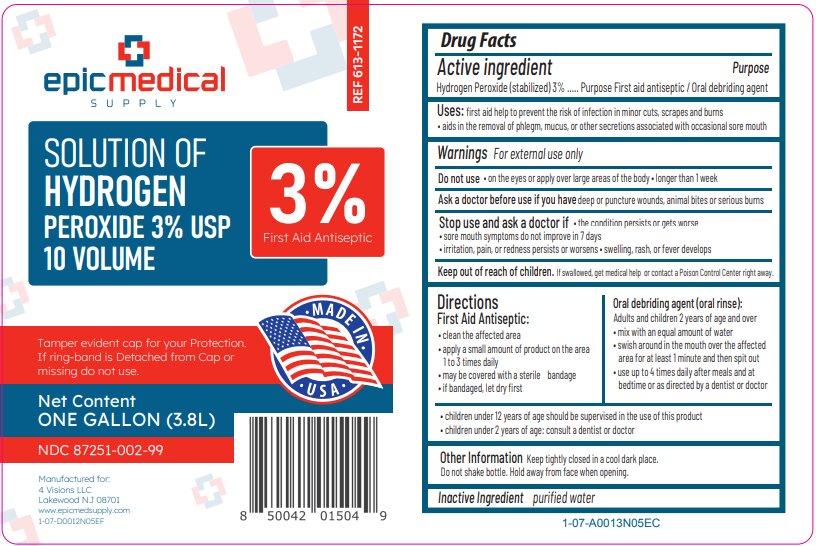 DRUG LABEL: Hydrogen Peroxide 3%
NDC: 87251-002 | Form: SOLUTION
Manufacturer: 4 Visions LLC
Category: otc | Type: HUMAN OTC DRUG LABEL
Date: 20260223

ACTIVE INGREDIENTS: HYDROGEN PEROXIDE 3 mL/100 mL
INACTIVE INGREDIENTS: WATER

Epic Medical Hydrogen Peroxide 3%, USP

Drug Facts

Active Ingredient

Hydrogen Peroxide (stabilized) 3%

Purpose

First Aid Antiseptic/Oral Debriding Agent

Uses

- first aid to help prevent the risk of infection in minor cuts, scrapes and burns
- aids in removal of phlegm, mucous, or other secretions associated with occasional sore mouth

Warnings

For external use only

Do not use

- in the eyes or apply over large areas of the body
- longer than 1 week

Ask a doctor before use if you havedeep puncture wounds, animal bites or serious burns.

Stop use and ask a doctor if

- the condition persists or gets worse
- sore mouth symptoms do not improve in 7 days
- irritation, pain, or redness persists or worsens
- swelling, rash, or fever develops

Keep out of reach of children.If swallowed, get medical help or contact a Poison Control Center right away (1-800-222-1222).

Directions

First Aid Antiseptic

- clean the affected area
- apply a small amount of product on the area 1 to 3 times a day
- may be covered with a sterile bandage
- if bandaged, let dry first

Oral Debriding Agent (oral rinse):

Adults and children 2 years of age & over:

- mix with an equal amount of water
- swish around in the mouth over the affected area for at least 1 minute and then spit out
- use up to 4 times daily after meals and at bedtime or as directed by a dentist or doctor

- children under 12 years of age should be supervised in the use of this product
- children under 2 years of age: consult a dentist or doctor

Other Information

- Keep tightly closed in a cool dark place
- Do not shake bottle
- Hold away from face when opening

Inactive Ingredient

Purified Water

Principal Display Panel One Gallon

NDC 87251-002-99

REF: 613-1172

epic medical supply

Solution of

Hydrogen Peroxide

3% USP 10 Volume

First Aid Antiseptic

Tamper evident cap for your protection. If ring band is detatche or missing do not use.

One Gallon (3.8L)

Made in USA

Manufactured for:

4 Visions LLC

Lakewood, NJ 08701

www.epicmedsupply.com